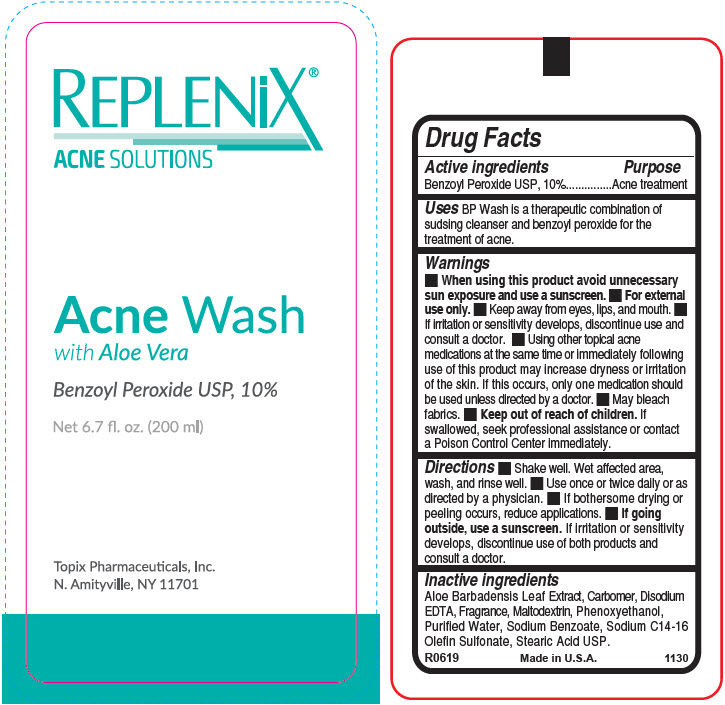 DRUG LABEL: REPLENIX ACNE 10% WASH PARABEN FREE WITH ALOE
NDC: 51326-113 | Form: LIQUID
Manufacturer: Topiderm, Inc.
Category: otc | Type: HUMAN OTC DRUG LABEL
Date: 20231204

ACTIVE INGREDIENTS: BENZOYL PEROXIDE 100 mg/1 mL
INACTIVE INGREDIENTS: ALOE VERA LEAF; CARBOMER HOMOPOLYMER, UNSPECIFIED TYPE; EDETATE DISODIUM ANHYDROUS; MALTODEXTRIN; PHENOXYETHANOL; WATER; SODIUM BENZOATE; SODIUM C14-16 OLEFIN SULFONATE; STEARIC ACID

REPLENIX® ACNE SOLUTIONS 10% WASH PARABEN FREE WITH ALOE

Drug Facts

Active ingredients

Benzoyl Peroxide USP, 10%

Purpose

Acne treatment

Uses

BP Wash is a therapeutic combination of sudsing cleanser and benzoyl peroxide for the treatment of acne.

Warnings

- When using this product avoid unnecessary sun exposure and use a sunscreen.
- For external use only.
- Keep away from eyes, lips, and mouth.
- If irritation or sensitivity develops, discontinue use and consult a doctor.
- Using other topical acne medications at the same time or immediately following use of this product may increase dryness or irritation of the skin. If this occurs, only one medication should be used unless directed by a doctor.
- May bleach fabrics.

- Keep out of reach of children. If swallowed, seek professional assistance or contact a Poison Control Center immediately.

Directions

- Shake well. Wet affected area, wash, and rinse well.
- Use once or twice daily or as directed by a physician.
- If bothersome drying or peeling occurs, reduce applications.
- If going outside, use a sunscreen. If irritation or sensitivity develops, discontinue use of both products and consult a doctor.

Inactive ingredients

Aloe Barbadensis Leaf Extract, Carbomer, Disodium EDTA, Fragrance, Maltodextrin, Phenoxyethanol, Purified Water, Sodium Benzoate, Sodium C14-16 Olefin Sulfonate, Stearic Acid USP.

PRINCIPAL DISPLAY PANEL - 200 ml Bottle Label

REPLENiX®
ACNE SOLUTIONS

Acne Wash
with Aloe Vera

Benzoyl Peroxide USP, 10%

Net 6.7 fl. oz. (200 ml)

Topix Pharmaceuticals, Inc.
N. Amityville, NY 11701